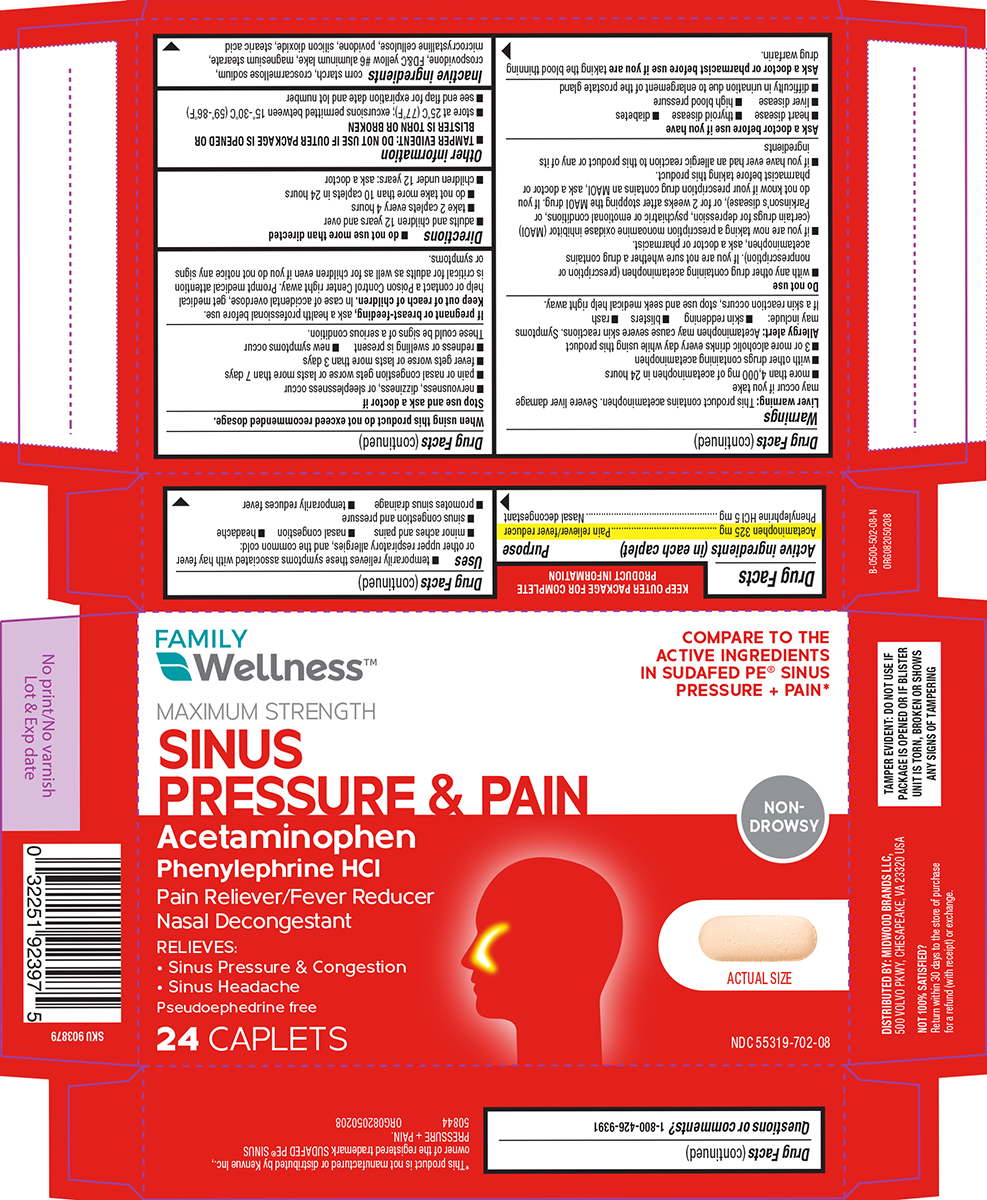 DRUG LABEL: Sinus Pressure and Pain
NDC: 55319-702 | Form: TABLET
Manufacturer: Family Dollar Services Inc
Category: otc | Type: HUMAN OTC DRUG LABEL
Date: 20260107

ACTIVE INGREDIENTS: ACETAMINOPHEN 325 mg/1 1; PHENYLEPHRINE HYDROCHLORIDE 5 mg/1 1
INACTIVE INGREDIENTS: STARCH, CORN; CROSCARMELLOSE SODIUM; CROSPOVIDONE, UNSPECIFIED; FD&C YELLOW NO. 6 ALUMINUM LAKE; MAGNESIUM STEARATE; MICROCRYSTALLINE CELLULOSE; POVIDONE, UNSPECIFIED; SILICON DIOXIDE; STEARIC ACID

Family Wellness 44-502

Active ingredients (in each caplet)

Acetaminophen 325 mg
Phenylephrine HCl 5 mg

Purpose

Pain reliever/fever reducer
Nasal decongestant

Uses

- temporarily relieves these symptoms associated with hay fever or other upper respiratory allergies, and the common cold:
  - minor aches and pains
  - nasal congestion
  - headache
  - sinus congestion and pressure
- promotes sinus drainage
- temporarily reduces fever

Warnings

Liver warning: This product contains acetaminophen. Severe liver damage may occur if you take

- more than 4,000 mg of acetaminophen in 24 hours
- with other drugs containing acetaminophen
- 3 or more alcoholic drinks every day while using this product

Allergy alert: Acetaminophen may cause severe skin reactions. Symptoms may include:

- skin reddening
- blisters
- rash

If a skin reaction occurs, stop use and seek medical help right away.

Do not use

- with any other drug containing acetaminophen (prescription or nonprescription). If you are not sure whether a drug contains acetaminophen, ask a doctor or pharmacist.
- if you are now taking a prescription monoamine oxidase inhibitor (MAOI) (certain drugs for depression, psychiatric or emotional conditions, or Parkinson’s disease), or for 2 weeks after stopping the MAOI drug. If you do not know if your prescription drug contains an MAOI, ask a doctor or pharmacist before taking this product.
- if you have ever had an allergic reaction to this product or any of its ingredients

Ask a doctor before use if you have

- heart disease
- thyroid disease
- diabetes
- liver disease
- high blood pressure
- difficulty in urination due to enlargement of the prostate gland

Ask a doctor or pharmacist before use if you are

taking the blood thinning drug warfarin.

When using this product

do not exceed recommended dosage.

Stop use and ask a doctor if

- nervousness, dizziness, or sleeplessness occur
- pain or nasal congestion gets worse or lasts more than 7 days
- fever gets worse or lasts more than 3 days
- redness or swelling is present
- new symptoms occur

These could be signs of a serious condition.

If pregnant or breast-feeding,

ask a health professional before use.

Keep out of reach of children.

In case of accidental overdose, get medical help or contact a Poison Control Center right away. Prompt medical attention is critical for adults as well as for children even if you do not notice any signs or symptoms.

Directions

- do not use more than directed
- adults and children 12 years and over
  - take 2 caplets every 4 hours
  - do not take more than 10 caplets in 24 hours
- children under 12 years: ask a doctor

Other information

- TAMPER EVIDENT: DO NOT USE IF OUTER PACKAGE IS OPENED OR BLISTER IS TORN OR BROKEN
- store at 25ºC (77ºF); excursions permitted between 15º-30ºC (59º-86ºF)
- see end flap for expiration date and lot number

Inactive ingredients

corn starch, croscarmellose sodium, crospovidone, FD&C yellow #6 aluminum lake, magnesium stearate, microcrystalline cellulose, povidone, silicon dioxide, stearic acid

Questions or comments?

1-800-426-9391

Principal display panel

FAMILY
Wellness™

COMPARE TO THE
ACTIVE INGREDIENTS
IN SUDAFED PE® SINUS
PRESSURE + PAIN*

MAXIMUM STRENGTH
SINUS
PRESSURE & PAIN

Acetaminophen
Phenylephrine HCl
Pain Reliever/Fever Reducer
Nasal Decongestant

RELIEVES:
• Sinus Pressure & Congestion
• Sinus Headache

Pseudoephedrine free

24 CAPLETS

NON
DROWSY

ACTUAL SIZE

NDC 55319-702-08

TAMPER EVIDENT: DO NOT USE IF
PACKAGE IS OPENED OR IF BLISTER
UNIT IS TORN, BROKEN OR SHOWS
ANY SIGNS OF TAMPERING

*This product is not manufactured or distributed by Kenvue Inc.,
owner of the registered trademark SUDAFED PE® SINUS
PRESSURE + PAIN.
50844 ORG082050208

DISTRIBUTED BY: MIDWOOD BRANDS LLC,
500 VOLVO PKWY, CHESAPEAKE, VA 23320 USA

NOT 100% SATISFIED?
Return within 30 days to the store of purchase
for a refund (with receipt) or exchange.

Family Wellness 44-502